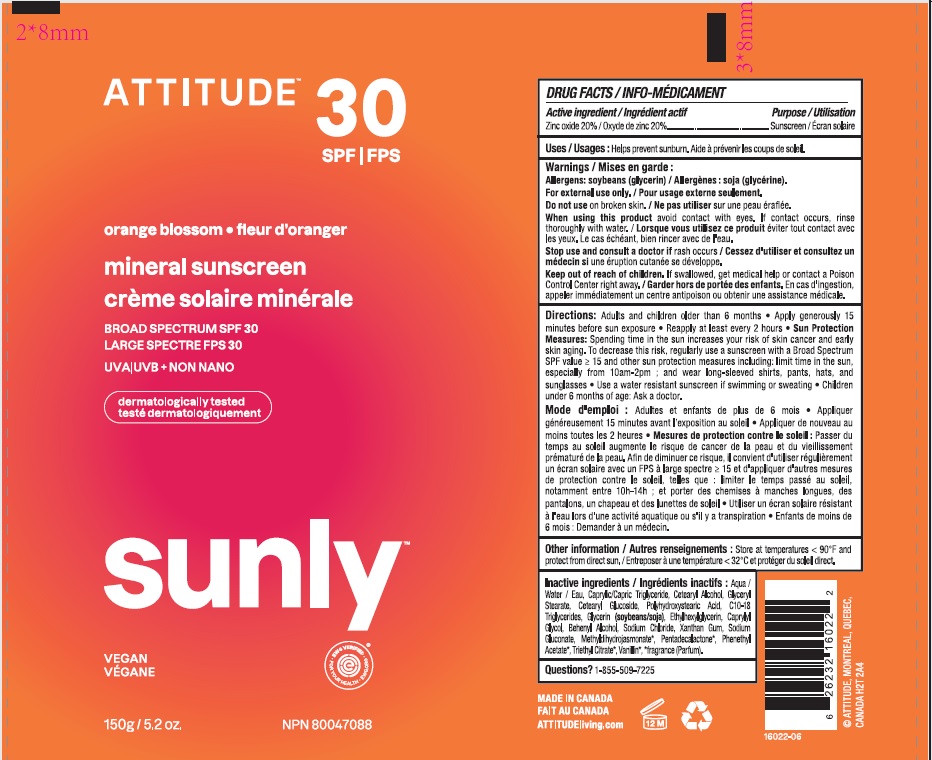 DRUG LABEL: Attitude mineral sunscreen orange blossom SPF 30
NDC: 61649-022 | Form: CREAM
Manufacturer: 9055-7588 Quebec Inc. DBA Attitude
Category: otc | Type: HUMAN OTC DRUG LABEL
Date: 20250113

ACTIVE INGREDIENTS: ZINC OXIDE 20 g/100 g
INACTIVE INGREDIENTS: PHENETHYL ACETATE; TRIETHYL CITRATE; VANILLIN; MEDIUM-CHAIN TRIGLYCERIDES; WATER; POLYHYDROXYSTEARIC ACID (2300 MW); CETOSTEARYL ALCOHOL; GLYCERYL MONOSTEARATE; CETEARYL GLUCOSIDE; ETHYLHEXYLGLYCERIN; GLYCERIN; C10-18 TRIGLYCERIDES; DOCOSANOL; SODIUM CHLORIDE; XANTHAN GUM; CAPRYLYL GLYCOL; SODIUM GLUCONATE; METHYL DIHYDROJASMONATE (SYNTHETIC); PENTADECALACTONE

Attitude®mineral sunscreen orange blossom SPF 30

Drug Facts

Active or medicinal ingredient

Zinc oxide (20%)

Purpose

Sunscreen

Use

Helps prevent sunburn

Warnings

Allergens: Soybeans (glycerin). For external use only.

Do not use on broken skin.

Stop use and ask a doctor ifrash occurs.

When using this product avoid contact with eyes. If contact occurs, rinse thoroughly with water.

Keep out of reach of children.If swallowed, get medical help or contact a Poison Control Center right away.

Directions

Adults and children older than 6 months.

- Apply generously 15 minutes before sun exposure.
- Reapply at least every 2 hours.
- Sun Protection Measures: Spending time in the sun increases your risk of skin cancer and early aging. To decrease this risk, regularly use a sunscreen with a Broad Spectrum SPFvalue of 15 or higher and other sun protection measures including: limit time in the sun, especially from 10am-2pm; and wear long-sleeved shirts, pants, hats and sunglasses.
- Use a water resistant sunscreen if swimming or sweating.
- Children under 6 months of age: Ask a doctor.

Inactive or non-medicinal ingredients

Aqua / Water / Eau, Caprylic/Capric Triglyceride, Cetearyl Glucoside, Glyceryl Stearate, Cetearyl Alcohol, Polyhydroxystearic Acid, C10-18 Triglycerides, Glycerin, Ethylhexylglycerin, Caprylyl Glycol, Behenyl Alcohol, Sodium Chloride, Xanthan Gum, Sodium Gluconate, Methyldihydrojasmonate*, Pentadecalactone*, Phenethyl Acetate*, Triethyl Citrate*, Vanillin*, *fragrance (Parfum).

Other Information

Store at temperatures below 90°F and protect from direct sun.

RECENT MAJOR CHANGES

Dosage and Administration: update of the directions

Questions? 1-855-709-7225

PRINCIPAL DISPLAY PANEL - 150 g Tube Label

ATTITUDE

30

SPF

Orange blossom

Mineral sunscreen

Broad spectrum SPF 30

UVA UVB + Non nano

SUNLY

Vegan

Dermatologically testesd

EWG Verified

NPN 80047088

150 g / 5.2 oz